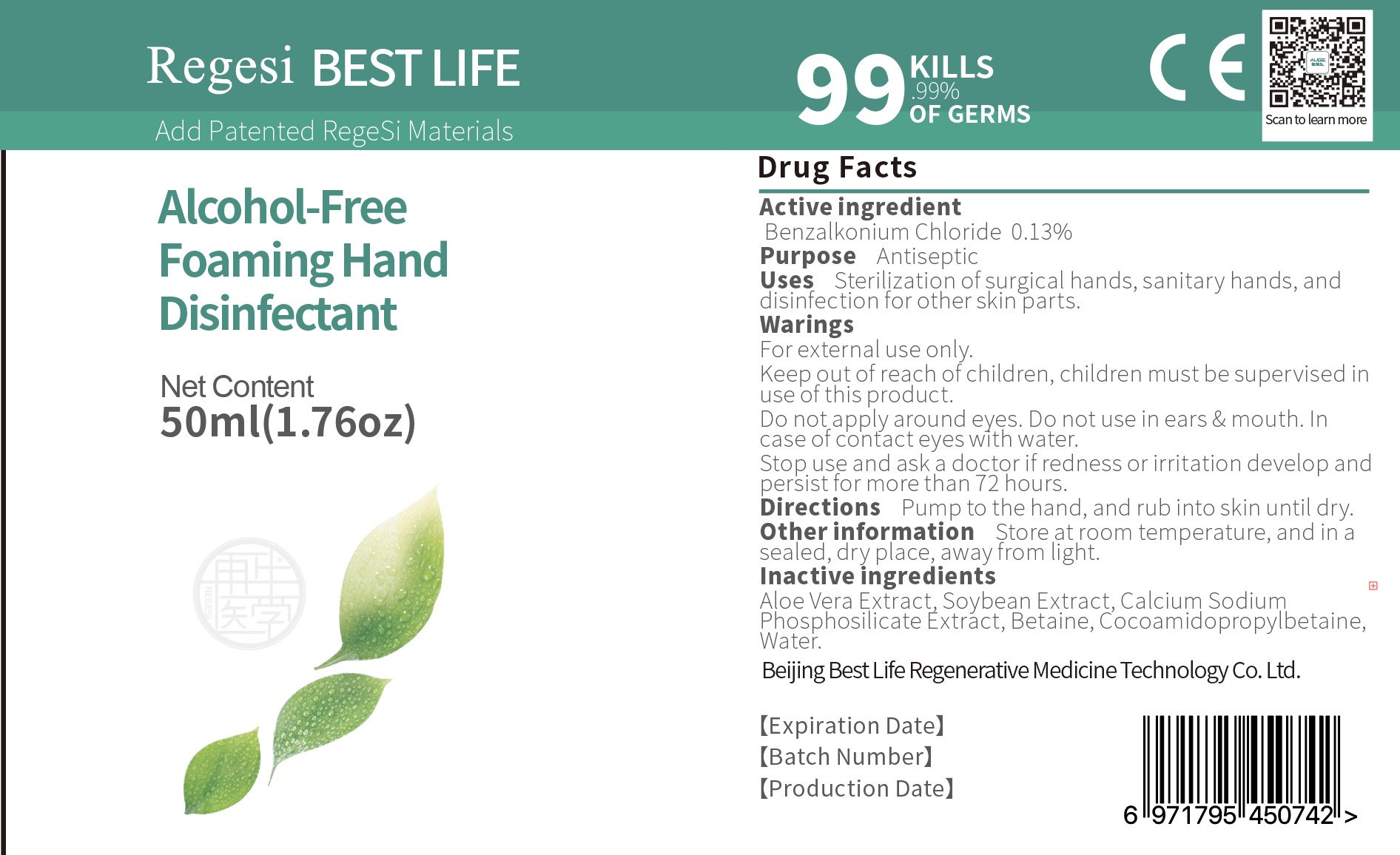 DRUG LABEL: Regesi Best Life Alcohol Free Foaming Hand Disinfectant
NDC: 74684-002 | Form: SOLUTION
Manufacturer: Beijing Best Life Regenerative Medicine Technology Co. Ltd.
Category: otc | Type: HUMAN OTC DRUG LABEL
Date: 20200414

ACTIVE INGREDIENTS: BENZALKONIUM CHLORIDE 0.13 g/100 mL
INACTIVE INGREDIENTS: SOYBEAN; WATER; CALCIUM SODIUM PHOSPHATE; BETAINE; ALOE VERA WHOLE

Drug Fact

Active Ingredient(s)

BENZALKONIUM CHLORIDE: 0.13%

Purpose

Antiseptic

Use

Use: Sterilization of surgical hands, sanitary hands, and disinfection of other parts

Warnings

Warning:

For external use only.

Do not apply around eyes, do not use in ears and mouth. In case of contact rinse with water

Stop use and ask a doctor if redness or irritation develop and persist for more than 72 hours

Keep out of reach of children. Chidren must be supervised in use of this product

Directions:

Pump to hands and rub into skin untill dry

Inactive ingredients

Inactive Ingredients: Aloe Vera Extract, Water, soybean extract, calcium sodium phophosilicate extract, Betane, cocoamidopropylbetaine

STORAGE AND HANDLING

Storage: Store in cool dry place away from light at room temperature